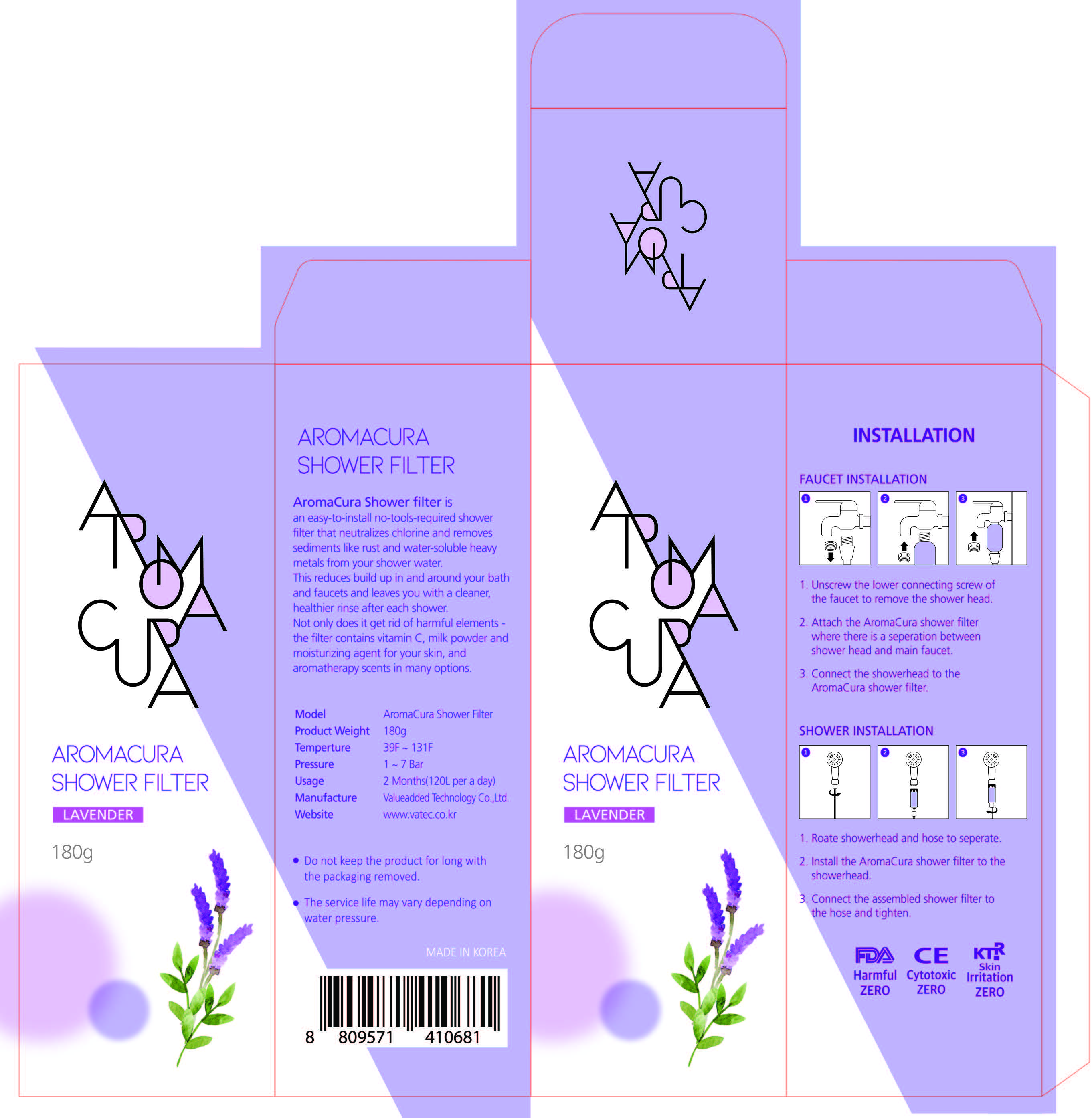 DRUG LABEL: AROMACURA SHOWER FILTER
NDC: 72832-0010 | Form: LIQUID
Manufacturer: Value Added Technology co., Ltd
Category: otc | Type: HUMAN OTC DRUG LABEL
Date: 20210105

ACTIVE INGREDIENTS: ASCORBIC ACID 39 g/100 g
INACTIVE INGREDIENTS: ICODEXTRIN; GLYCERIN

Drug Facts

ACTIVE INGREDIENT

Ascorbic Acid

INACTIVE INGREDIENT

Dextrin, Keltrol, Glycerine, Nonfat dry milk, Food coloring, Perfume

PURPOSE

Skin Protectant

keep out of reach of the children

INDICATIONS AND USAGE

Faucet Installation

1. Unscrew the lower connecting screw of the faucet to remove the shower head.

2. Attach the AromaCura shower filter where there is a separation between shower head and main faucet.

3. Connect the showerhead to the AromaCura shower filter.

Shower Installation

1. Rotate showerhead and hose to separate.

2. Install the AromaCura shower filter to the showerhead.

3. Connect the assembled shower filter to the hose and tighten.

WARNINGS

- Do not keep the product for long with the packaging removed.
- The service life may vary depending on water pressure.

DOSAGE AND ADMINISTRATION

for external use only